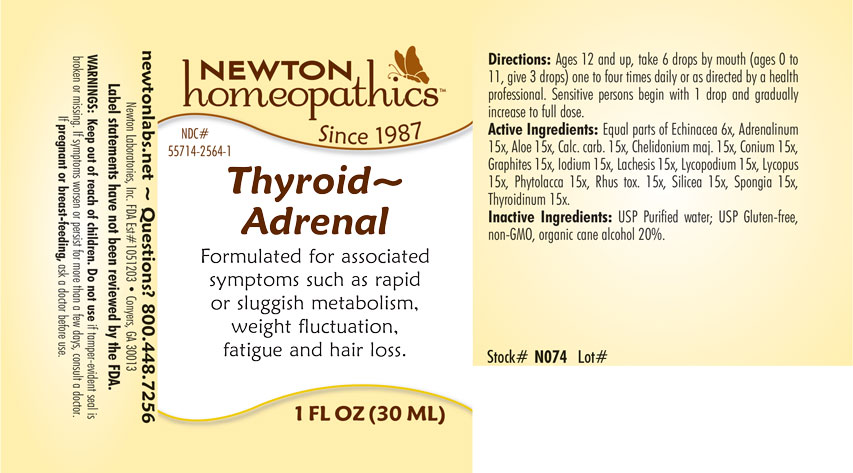 DRUG LABEL: Thyroid-Adrenal
NDC: 55714-2564 | Form: LIQUID
Manufacturer: Newton Laboratories, Inc.
Category: homeopathic | Type: HUMAN OTC DRUG LABEL
Date: 20201203

ACTIVE INGREDIENTS: EPINEPHRINE 15 [hp_X]/1 mL; THYROID, UNSPECIFIED 15 [hp_X]/1 mL; ALOE 15 [hp_X]/1 mL; OYSTER SHELL CALCIUM CARBONATE, CRUDE 15 [hp_X]/1 mL; CHELIDONIUM MAJUS 15 [hp_X]/1 mL; CONIUM MACULATUM FLOWERING TOP 15 [hp_X]/1 mL; GRAPHITE 15 [hp_X]/1 mL; IODINE 15 [hp_X]/1 mL; LACHESIS MUTA VENOM 15 [hp_X]/1 mL; LYCOPODIUM CLAVATUM SPORE 15 [hp_X]/1 mL; LYCOPUS VIRGINICUS 15 [hp_X]/1 mL; PHYTOLACCA AMERICANA ROOT 15 [hp_X]/1 mL; TOXICODENDRON PUBESCENS LEAF 15 [hp_X]/1 mL; SILICON DIOXIDE 15 [hp_X]/1 mL; SPONGIA OFFICINALIS SKELETON, ROASTED 15 [hp_X]/1 mL; ECHINACEA, UNSPECIFIED 6 [hp_X]/1 mL
INACTIVE INGREDIENTS: WATER; ALCOHOL

Thyroid 2564L

OTC - KEEP OUT OF REACH OF CHILDREN SECTION

Keep out of reach of children.

OTC - PREGNANCY OR BREAST FEEDING SECTION

If pregnant or breast-feeding, ask a doctor before use.

WARNINGS SECTION

WARNINGS: Keep out of reach of children. Do not use if tamper-evident seal is broken or missing. If symptoms worsen or persist for more than a few days, consult a doctor. If pregnant or breast-feeding, ask a doctor before use.

QUESTIONS SECTION

newtonlabs.net – Questions? 800.448.7256

Newton Laboratories, Inc. FDA Est # 1051203 - Conyers, GA 30013

INACTIVE INGREDIENT SECTION

Inactive Ingredients: USP Purified Water; USP Gluten-free, non-GMO, organic cane alcohol 20%.

OTC - PURPOSE SECTION

Formulated for associated symptoms such as rapid or sluggish metabolism, weight fluctuation, fatigue and hair loss.

OTC - ACTIVE INGREDIENT SECTION

Equal parts of Echinacea 6x, Aloe 15x, Calcarea carbonica 15x, Chelidonium majus 15x, Conium maculatum 15x, Graphites 15x, Iodium 15x, Lachesis mutus 15x, Lycopodium clavatum 15x, Lycopus virginicus 15x, Phytolacca decandra 15x, Rhus toxicodendron 15x, Silicea 15x, Spongia tosta 15x, Adrenalinum 15x, Thyroidinum 15x.

DOSAGE & ADMINISTRATION SECTION

Directions: Ages 12 and up, take 6 drops by mouth (ages 0 to 11, give 3 drops) one to four times daily or as directed by a health professional. Sensitive persons begin with 1 drop and gradually increase to full dose.

INDICATIONS & USAGE SECTION

Formulated for associated symptoms such as rapid or sluggish metabolism, weight fluctuation, fatigue and hair loss.